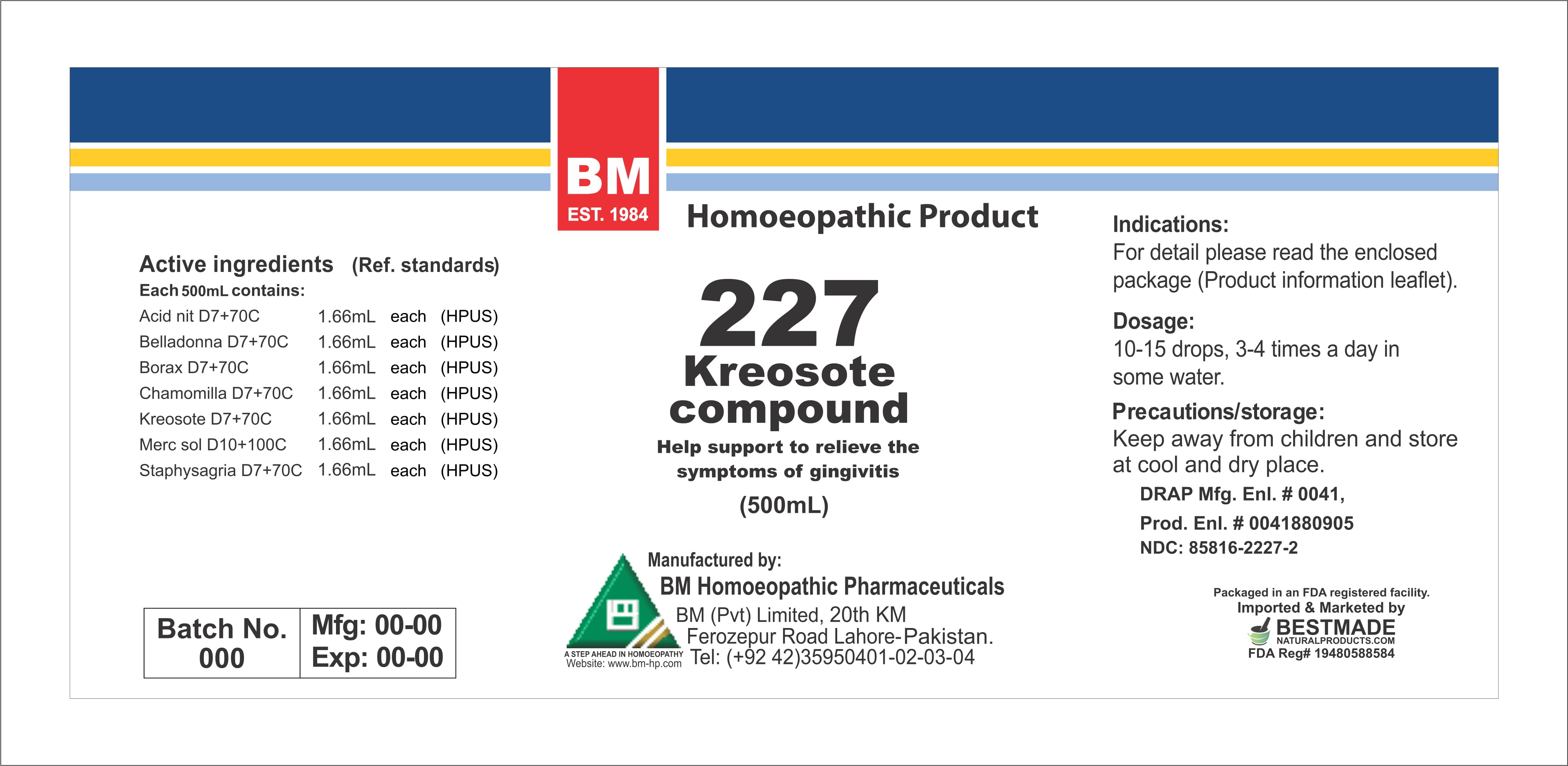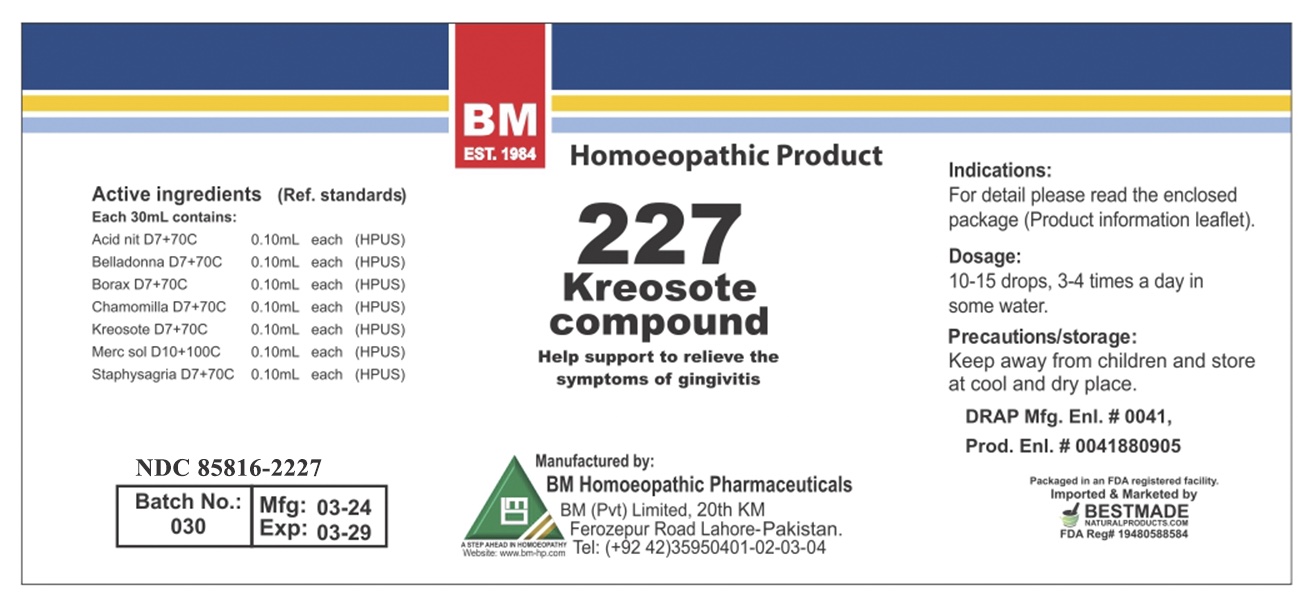 DRUG LABEL: KREOSOTE
NDC: 85816-2227 | Form: LIQUID
Manufacturer: BM Private Limited
Category: homeopathic | Type: HUMAN OTC DRUG LABEL
Date: 20260215

ACTIVE INGREDIENTS: SODIUM BORATE 7 [hp_X]/1 mL; ATROPA BELLADONNA 7 [hp_X]/1 mL; NITRIC ACID 7 [hp_X]/1 mL; WOOD CREOSOTE 7 [hp_X]/1 mL; MERCURIUS SOLUBILIS 10 [hp_X]/1 mL; CHAMOMILE 7 [hp_X]/1 mL; DELPHINIUM STAPHISAGRIA SEED 7 [hp_X]/1 mL
INACTIVE INGREDIENTS: ALCOHOL 0.96 mL/1 mL

HOMEOPATHIC LIQUID KREOSOTE/ BM227

DOSAGE AND ADMINISTRATION

10-15 drops, 3-4 times a day in some water

ACTIVE INGREDIENT

acid nit, belladonna, borax, chamomilla, kreosote, merc sol, staphysagria

INACTIVE INGREDIENT

ALCOHOL

INDICATIONS AND USAGE

For detail, please read the enclosed package (product information leaflet)

PURPOSE

For detail, please read the enclosed package (product information leaflet)

KEEP OUT OF REACH OF CHILDREN

Precautions/storage:
Keep away from children and store at cool and dry place.

WARNINGS

Precautions/storage:
Keep away from children and store at cool and dry place.

Package 1

Package 2